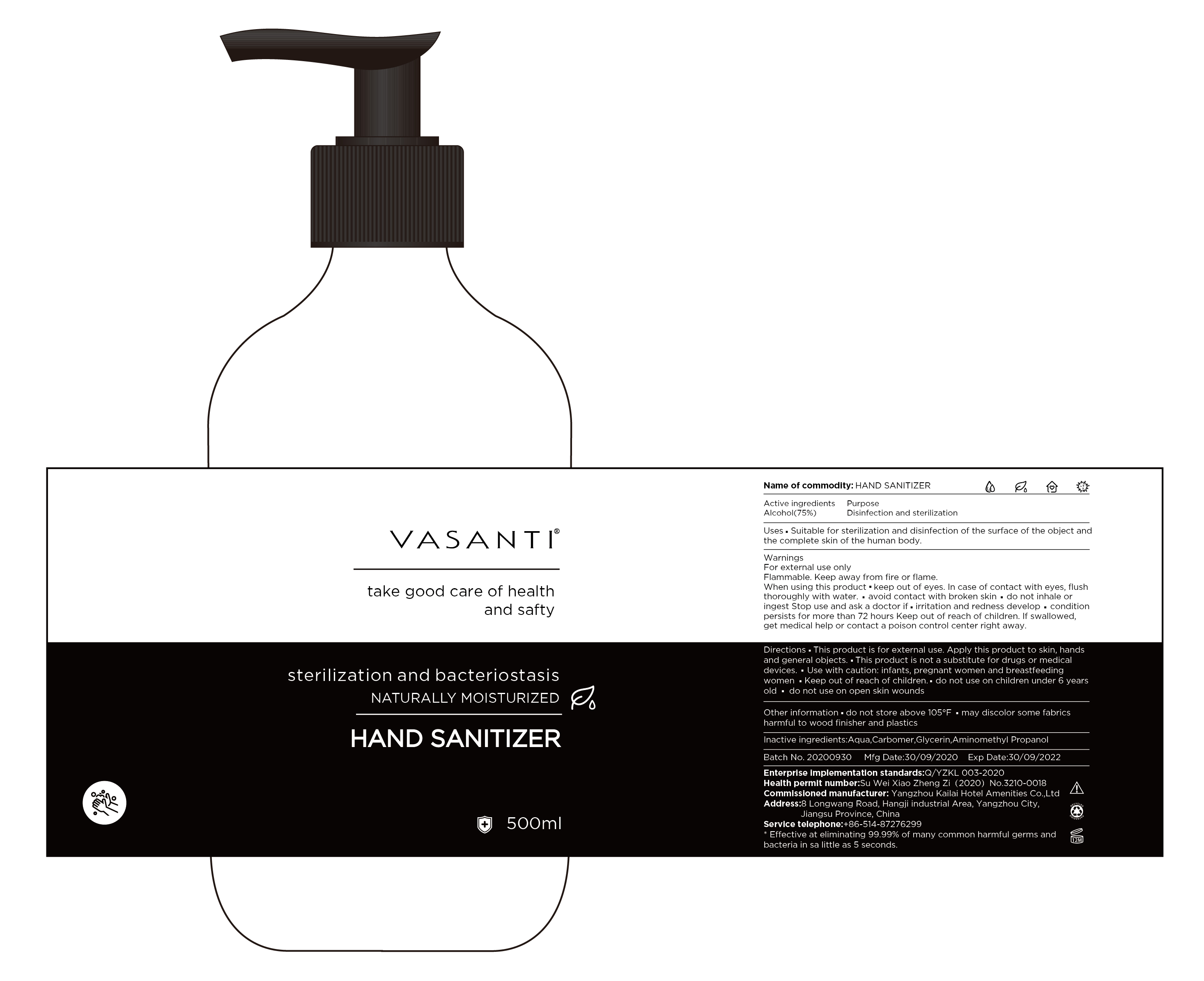 DRUG LABEL: VASANTI HAND SANITIZER
NDC: 80532-001 | Form: SOLUTION
Manufacturer: Yangzhou Kailai Hotel Amenities Co., Ltd.
Category: otc | Type: HUMAN OTC DRUG LABEL
Date: 20201022

ACTIVE INGREDIENTS: ALCOHOL 75 mL/100 mL
INACTIVE INGREDIENTS: GLYCERIN; WATER; CARBOMER 940; AMINOMETHYL PROPANEDIOL

80532-001

Active Ingredient(s)

Alcohol 75%

Purpose

Disinfection and Sterilization

Use

Suitable for disinfection and sterilization of the surface of the objects and the complete skin of the human body

Warnings

For external use only.

Flammable. Keep away from fire or flame

Discontinue if skin becomes irritated and ask a doctor

When using this product, keep out of eyes. In case of contact with eyes, flush thoroughly with water

Do not inhale or ingest

Avoid contact with broken skin

Stop use and ask a doctor if irritation and redness develop and condition persists for more than 72 hours

Keep out of reach of children. If swallowed, get medical help or contact a Poison Control Center right away.

Directions

This product is for external use. Apply this product to skin, hands, and general objects.

This product is not a substitute for drugs or medical devices.

Use with caution: Infants, pregnant women, and breast feeding women

Keep out of reach of children

Do not use on children under 6 years old

Do not use on open skin wounds

Other information

Do not store above 105F

May discolor some fabrics

Harmful to wooden finishes and plastics

Inactive ingredients

Water, Glycerin, Carbomer, Aminomethyl Propanol